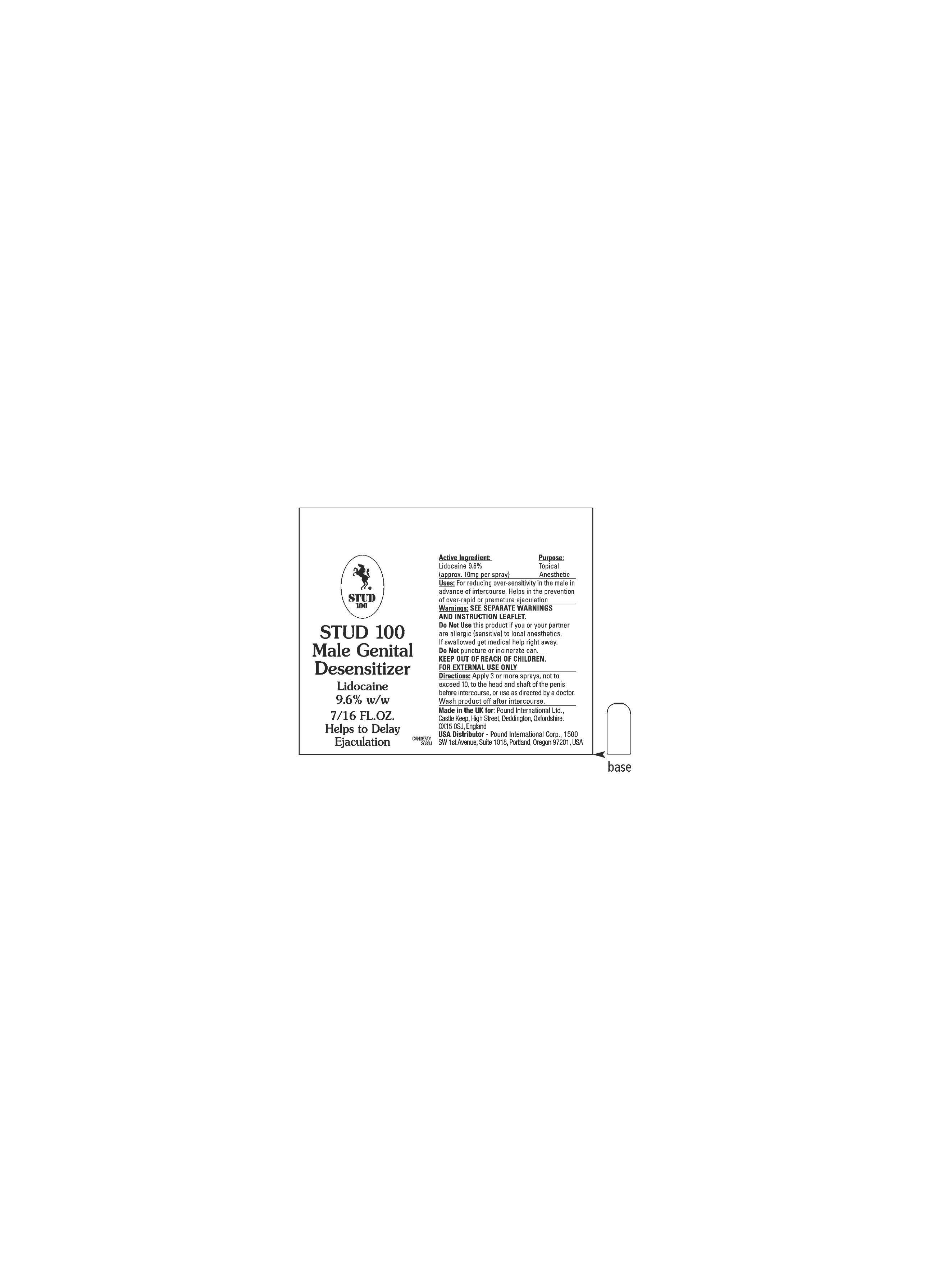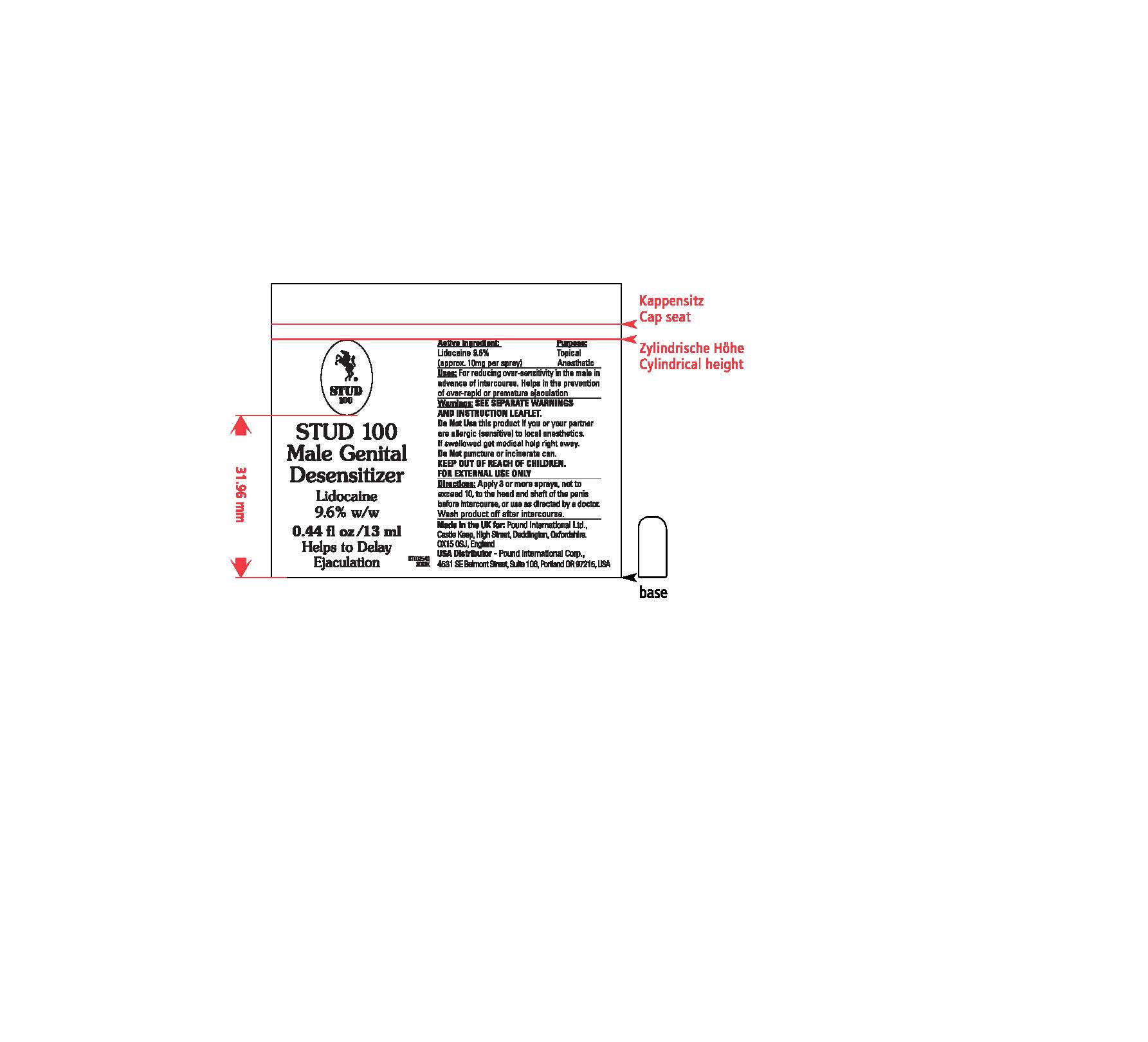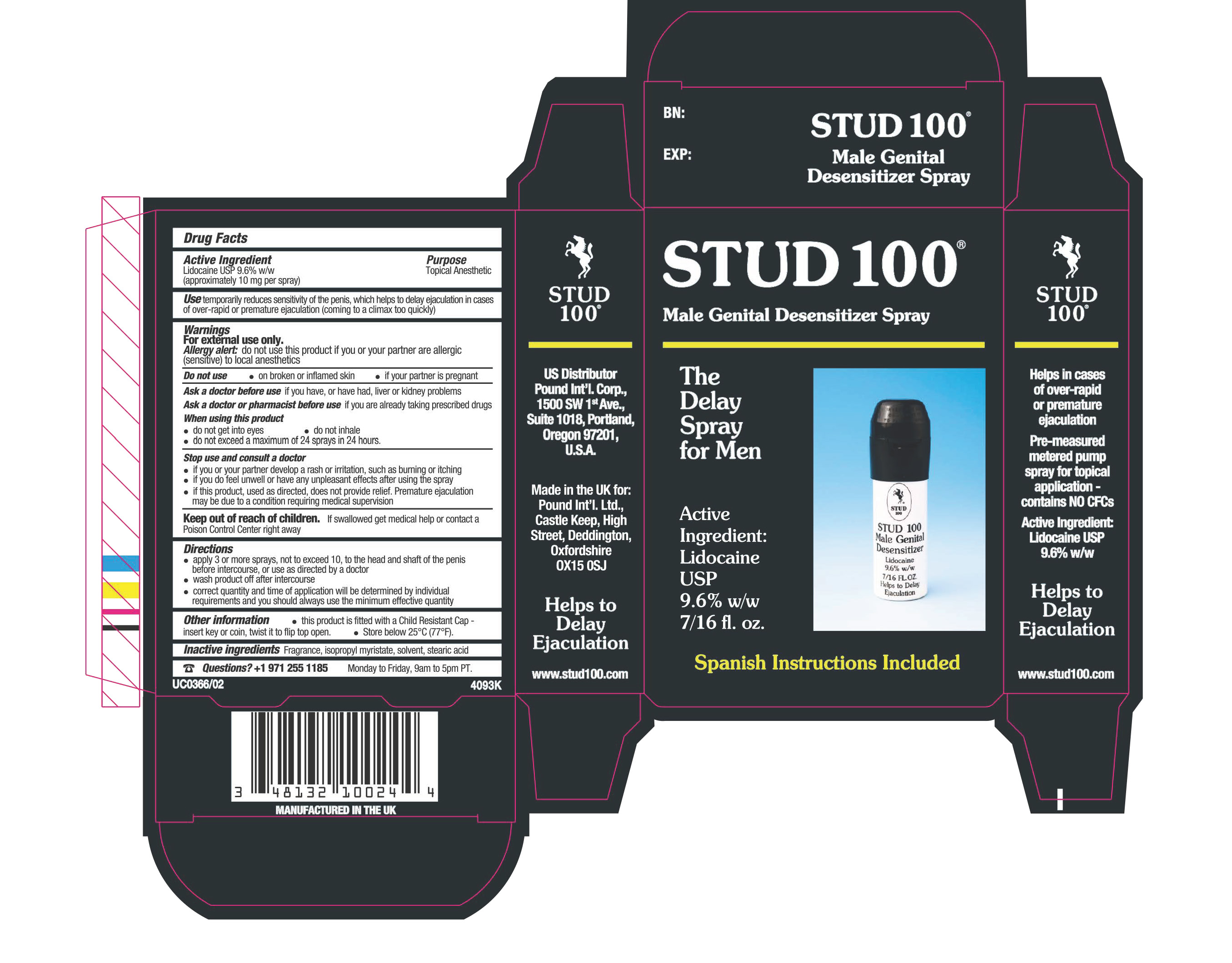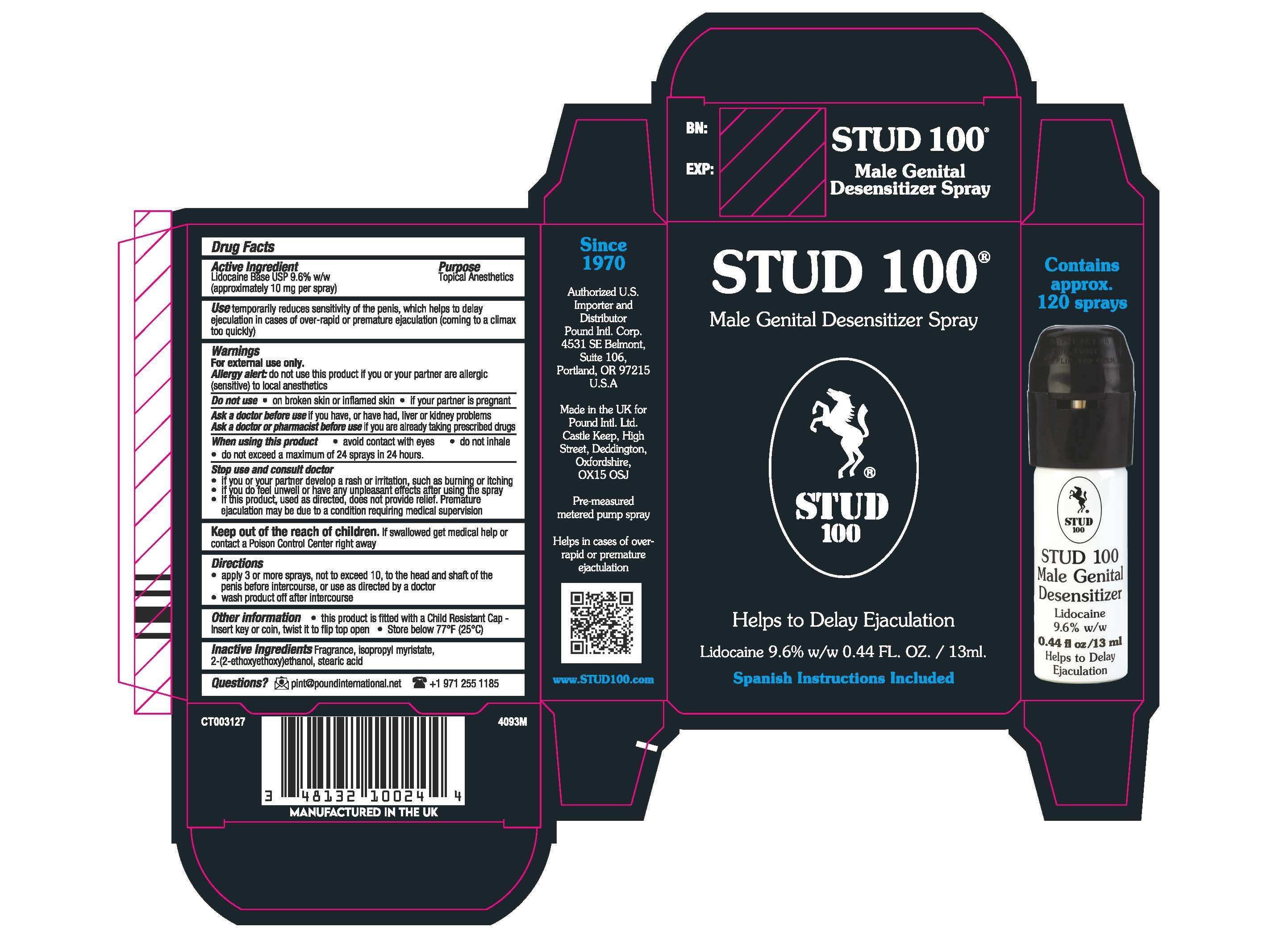 DRUG LABEL: Male Genital Desensitizer
NDC: 57707-050 | Form: SPRAY, METERED
Manufacturer: Pound International Corp
Category: otc | Type: HUMAN OTC DRUG LABEL
Date: 20241219

ACTIVE INGREDIENTS: LIDOCAINE 9.6 mg/100 mL
INACTIVE INGREDIENTS: 2-(2-ETHYLHEXYLOXY)ETHANOL; ISOPROPYL MYRISTATE; STEARIC ACID

Stud 100 Male Desensitizer

Active Ingredient Purpose

Lidocaine Base 9.6% w/w (approximately 10 mg per spray) Topical Anesthetic

Use

temporarily reduces sensitivity of the penis, which helps to delay ejaculation in cases of over-rapid or premature ejaculation (coming to a climax too quickly)

Keep out of reach of children. If swallowed get medical help or contact a Poison Control Center right away.

INDICATIONS AND USAGE

Stop and consult a doctor

if you or your partner develop a rash or irritation, such as burning or itching

if you do feel unwell or have any unpleasant effects after using the spray

If this product, used as directed, does not provide relief. Premature ejaculation may be due to a condition requiring medical supervision

Warnings

For external use only

Allergy alert: do not use this product if you or your partner are allergic (sensitive) to local Anesthetics.

Do not use - on broken or inflamed skin -if your partner is pregnant

Ask a doctor before use if you have, or ever had, liver or kidney problems

Ask a doctor or pharmacist before use if you are already taking prescribed drugs

when using this product

- do not get into eyes

- do not inhale

- do not exceed 24 sprays in 24 hours

Directions

-apply 3 or more sprays, not to exceed 10, to the head and shaft of the penis before intercourse, or as directed by a doctor

-wash product after intercourse

-correct quantity and time of application will be determined by individual requirements and you should always use the minimum effective quantity

Inactive Ingredients

Fragrance, isopropyl myristate, solvent, stearic acid

PACKAGE LABEL

Stud 100 Male Genital Desensitizer Spray

The Delay Spray for Men

Active ingredient

Lidocaine Base USP

9.6% w/w 7/16 fl. oz